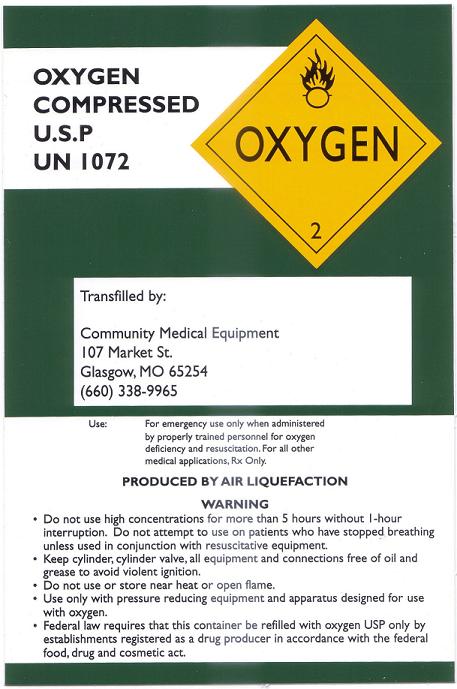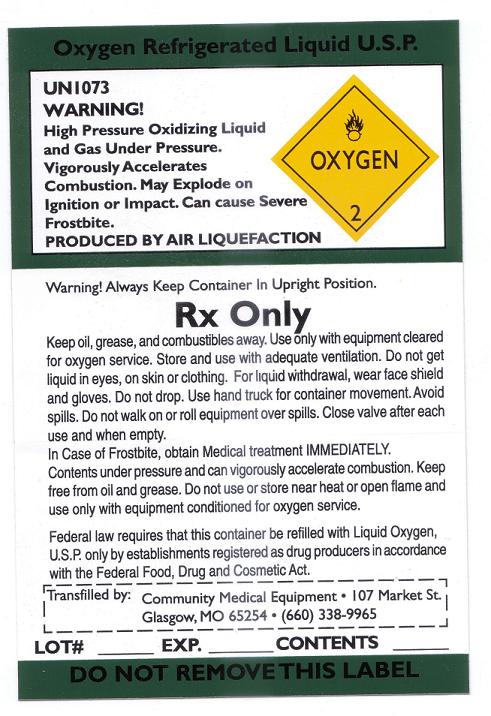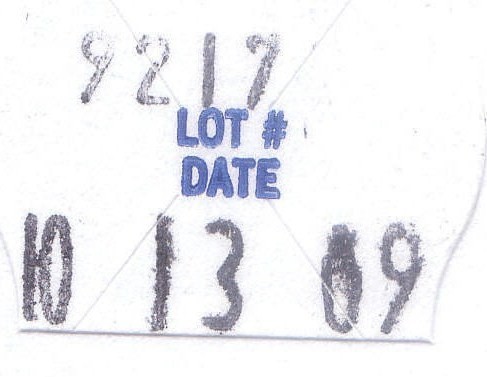 DRUG LABEL: Oxygen
NDC: 63983-0001 | Form: GAS
Manufacturer: Community Medical Equipment
Category: prescription | Type: HUMAN PRESCRIPTION DRUG LABEL
Date: 20091022

ACTIVE INGREDIENTS: Oxygen 99 L/100 L

Oxygen